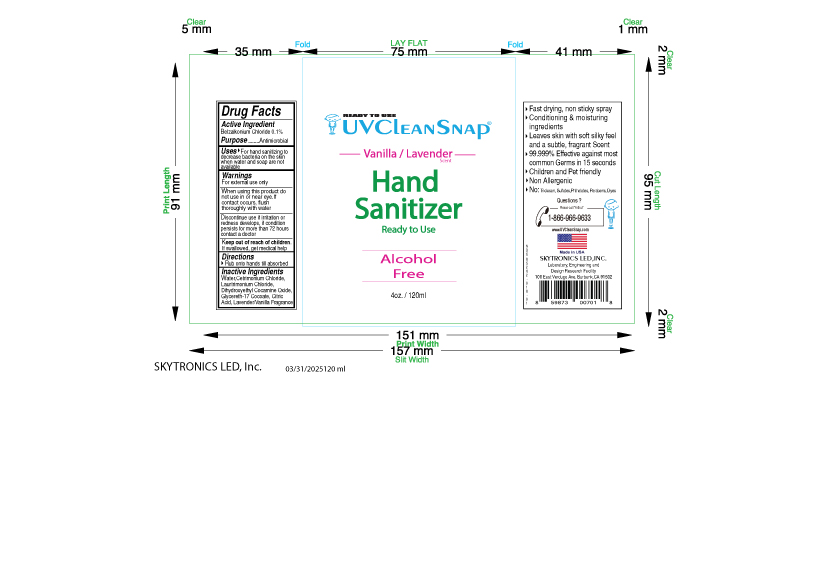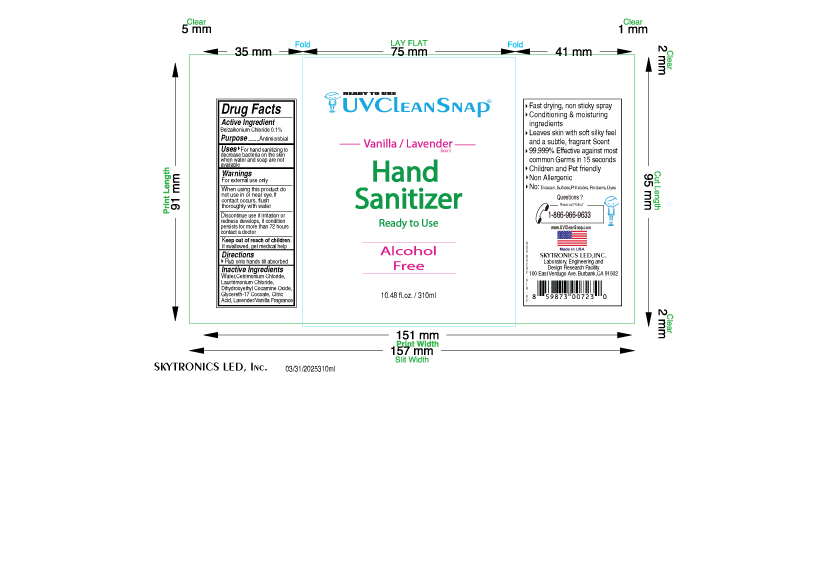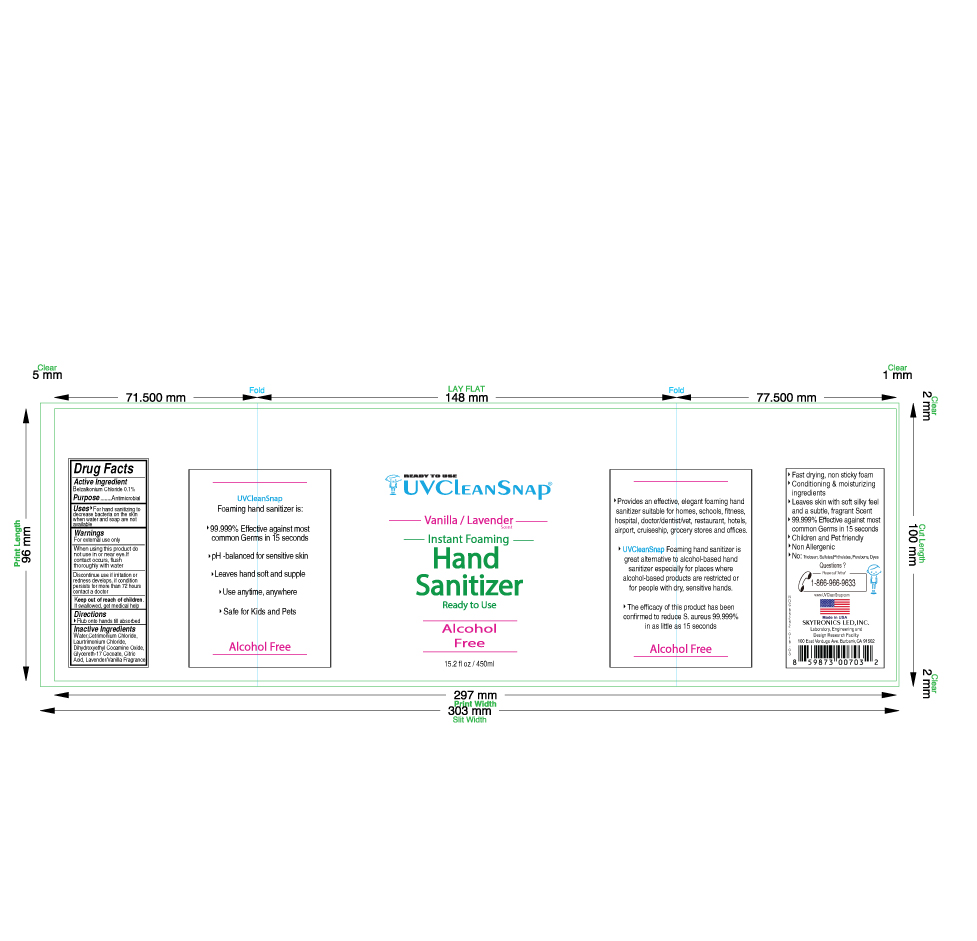 DRUG LABEL: UVCleanSnap Hand Sanitizer
NDC: 85262-018 | Form: SPRAY, METERED
Manufacturer: Skytronics LED, Inc.
Category: otc | Type: HUMAN OTC DRUG LABEL
Date: 20250406

ACTIVE INGREDIENTS: BENZALKONIUM CHLORIDE 1 mg/1 mL
INACTIVE INGREDIENTS: VANILLA BEAN; CETRIMONIUM CHLORIDE; LAURTRIMONIUM CHLORIDE; CITRIC ACID; GLYCERETH-17 COCOATE; WATER; DIHYDROXYETHYL COCAMINE OXIDE; FRAGRANCE LAVENDER ORC1800979

UVCleanSnap Hand Sanitizer

Active Ingredient

BENZALKONIUM CHLORIDE – 0.1% w/v

Purpose

Antimicrobial

Uses

For hand sanitizing to decrease bacteria on the skin when water and soap are not available

Warnings

For external use only

When using this product do not use in or near eye. If contact occurs, flush thoroughly with water

Discontinue use if irritation or redness develops, if condition persists for more than 72 hours contact a doctor

Keep out of reach of Children

If swallowed, get medical help

Directions

Rub onto hands till absorbed

Inactive Ingredients

WATER (UNII: 059QF0KO0R),

CETRIMONIUM CHLORIDE (UNII: UC9PE95IBP),

LAURTRIMONIUM CHLORIDE (UNII: A81MSI0FIC),

DIHYDROXYETHYL COCAMINE OXIDE (UNII: 8AR51R3BL5),

GLYCERETH-17 COCOATE (UNII: 3057VPT0KC),

CITRIC ACID MONOHYDRATE (UNII: 2968PHW8QP),

VANILLA BEAN (UNII: Q74T35078H),

FRAGRANCE LAVENDER ORC1800979 (UNII: 1B40MIN2W5)

Package Labeling:

120ml

310ml

450ml